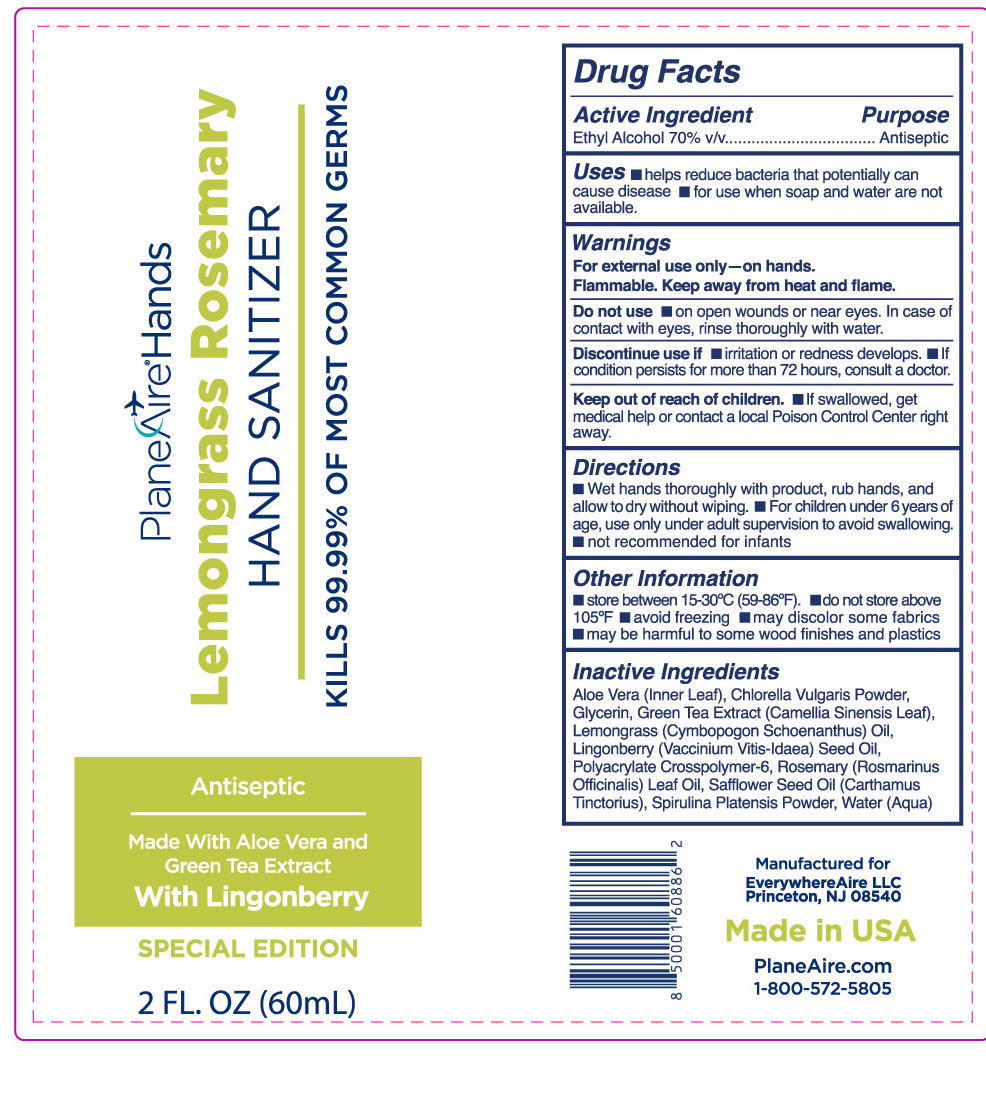 DRUG LABEL: PlaneAire Hands
NDC: 80335-116 | Form: LOTION
Manufacturer: EverywhereAire LLC
Category: otc | Type: HUMAN OTC DRUG LABEL
Date: 20231220

ACTIVE INGREDIENTS: ALCOHOL 70 mL/100 mL
INACTIVE INGREDIENTS: WATER; SPIRULINA PLATENSIS; ALOE VERA LEAF POLYSACCHARIDES; ROSEMARY OIL; SAFFLOWER OIL; EAST INDIAN LEMONGRASS OIL; LINGONBERRY SEED OIL; CHLORELLA VULGARIS; GREEN TEA LEAF; GLYCERIN; SODIUM POLYACRYLATE (2500000 MW)

PlaneAire Hands lotion with lemongrass, rosemary, aloe vera inner leaf, green tea, safflower oleosomes, chlorella, and spirulina

Purpose

Antiseptic

ACTIVE INGREDIENT

Ethyl alcohol 70 % v/v

INDICATIONS AND USAGE

- helps reduce bacteria that potentially can cause disease
- for use when soap and water are not available

Warnings

For external use only- on hands

Flammable. Keep away from heat and flame.

Do not use

- on open wounds or near eyes. In case of contact with eyes, rinse thoroughly with watwer.

Discontinue Use if

- irritation or redness develops
- If cindiction persists for more than 72 hours, consult a doctor.

Keep out of reach of children

If swallowed, get medical help or contact a local Poison Control Center right away.

Directions

- Wet hands thoroughly with product, rub hands, and allow to dry without wiping
- For children under 6 years of age, use only under adult supervision to avoid swallowing.
- not recommended for infants

Other Information

- store between 15-30 C (59-86 F)
- do not store above 105 F
- avoid freezing
- may discolor some fabrics
- may be harmful to some wood finishes and plastics

Dosage and Administration

Section name changed and sequence changed

Other Information

- store between 15-30 C
- do not store above 105 F
- avoid freezing
- may discolor some fabrics
- may be harmful to some wood finishes and plastics

Inactive Ingredients

Aloe Vera (Inner Leaf), Chlorella Vulgaris Powder, Glycerin, Green Tea Extract (Camellia Sinensis Leaf), Lemongrass (Cymbopogon Schoenanthus) Oil, Lingonberry (Vaccinium Vitis-Idaea) Seed Oil, Polyacrylate Crosspolymer-6, Rosemary (Rosmarinus Officinalis) Leaf Oil, Safflower Seed Oil (Carthamus Tinctorius), Spirulina Platensis Powder, Water (Aqua)